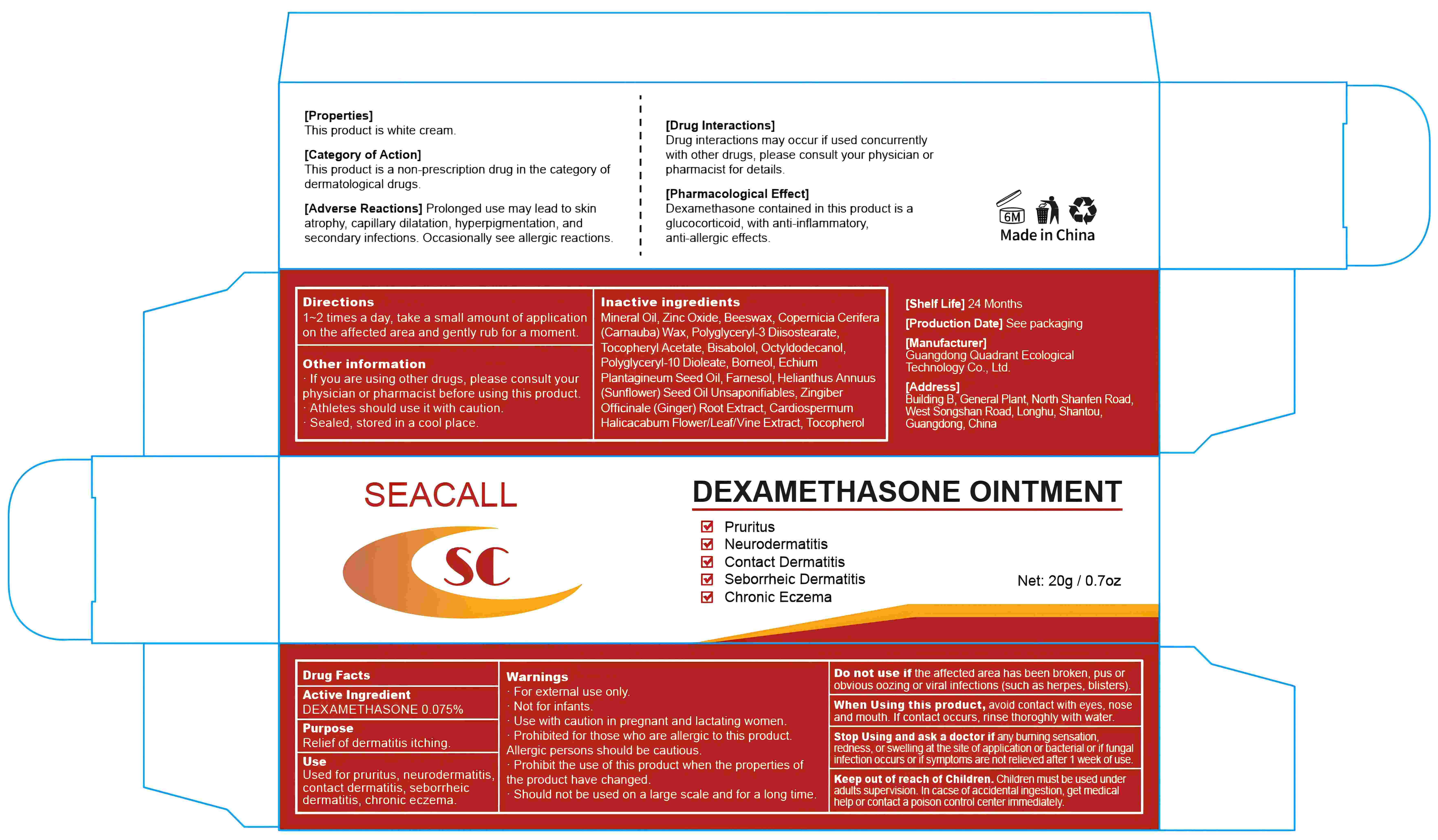 DRUG LABEL: Seacall Dexamethasone Ointment.
NDC: 76986-004 | Form: OINTMENT
Manufacturer: Guangdong Quadrant Ecological Technology Co., Ltd.
Category: otc | Type: HUMAN OTC DRUG LABEL
Date: 20251015

ACTIVE INGREDIENTS: DEXAMETHASONE 0.075 g/100 g
INACTIVE INGREDIENTS: ECHIUM PLANTAGINEUM SEED OIL; TOCOPHEROL; POLYGLYCERYL-10 DIOLEATE; LEVOMENOL; BORNEOL; FARNESOL; GINGER; CARDIOSPERMUM HALICACABUM FLOWERING TOP; POLYGLYCERYL-3 DIISOSTEARATE; SUNFLOWER OIL UNSAPONIFIABLES; MINERAL OIL; ZINC OXIDE; CARNAUBA WAX; YELLOW WAX; .ALPHA.-TOCOPHEROL ACETATE; OCTYLDODECANOL

76986-004 Active

Active Ingredient

Dexamethasone 0.075%

Purpose

Relief of dermatitis itching.

Use

Used for pruritus, neurodermatitis, contact dermatitis, seborrheic dermatitis, chronic eczema.

Warnings

For external use only.
Not for infants.
Use with caution in pregnant and lactating women.
Prohibited for those who are allergic to this product.
Allergic persons should be cautious.
Prohibit the use when the properties of the product have changed.
Should not be used on a large scale and for a long time.

Do not use

If the affected area has been broken, pus or obvious oozing or viral infections (such as herpes, blisters).

When Using

Avoid contact with eyes, nose, and mouth. If contact occurs, rinse thoroughly with water.

Stop Use

Ask a doctor if any burning sensation, redness, or swelling at the site of application or bacterial or fungal infections occurs or if symptoms are not relieved after 1 week of use.

Keep Oot Of Reach Of Children

Children must be used under adult supervision. In case of accidental ingestion, get medical help or contact a poison control center immediately.

Directions

1-2 times a day, take a small amount of application on the affected area and gently rub for a moment.

Other information

If you are using other drugs, please consult your physician or pharmacist before using this product.
Athletes should use it with caution.
Sealed, stored in a cool place.

Inactive ingredients

Mineral Oil, Zinc Oxide, Beeswax, Copernicia Cerifera (Carnauba) Wax, Polyglyceryl-3 Diisostearate, Tocopheryl Acetate, Bisabolol, Octyldodecanol, Polyglyceryl-10 Dioleate, Borneol, Echium Plantagineum Seed Oil, Farnesol, Helianthus Annuus (Sunflower) Seed Oil Unsaponifiables, Zingiber Officinale (Ginger) Root Extract, Cardiospermum Halicacabum Flower/Leaf/Vine Extract, Tocopherol.